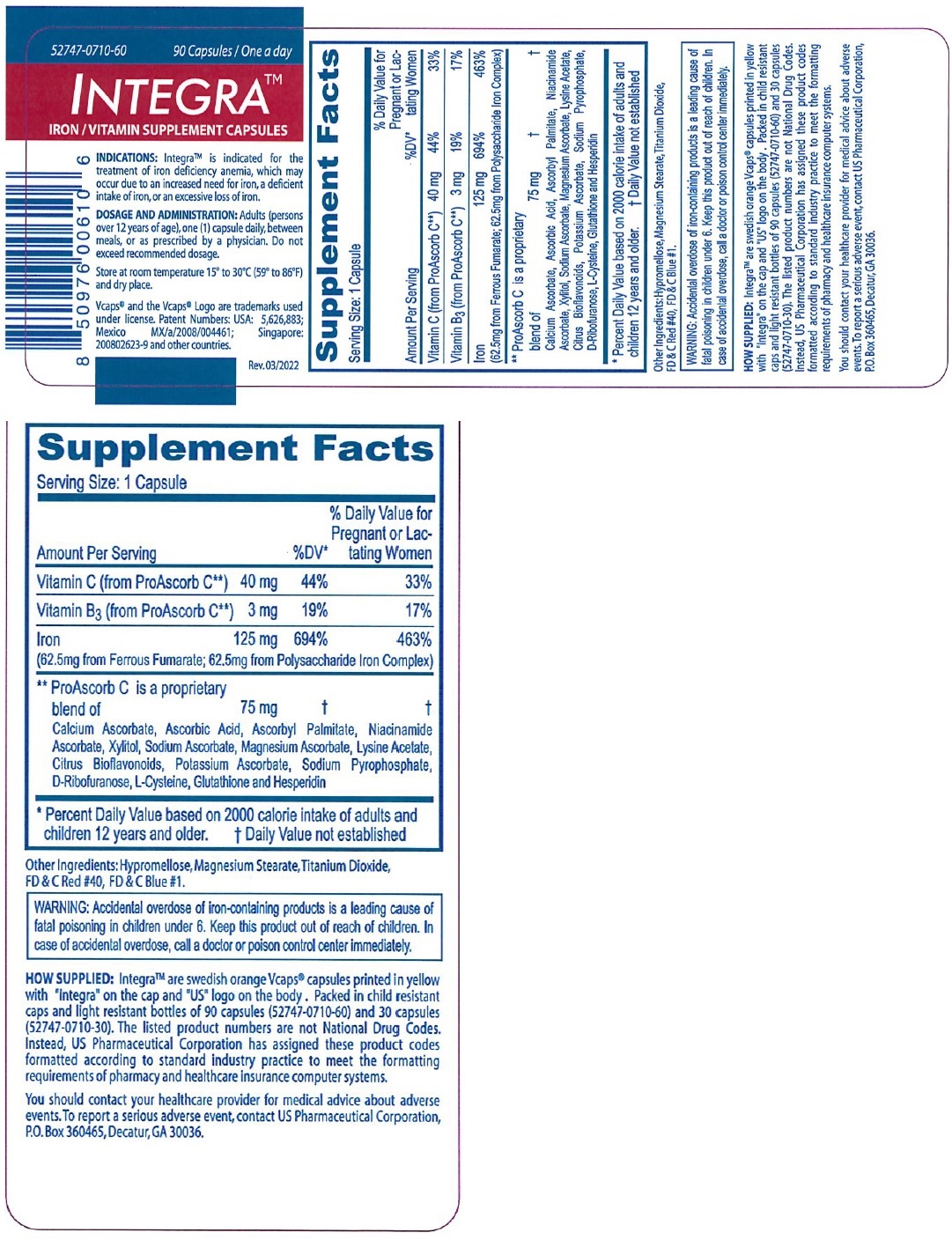 DRUG LABEL: Integra
NDC: 52747-710 | Form: CAPSULE
Manufacturer: U.S. Pharmaceutical Corporation
Category: other | Type: Dietary Supplement
Date: 20230614

ACTIVE INGREDIENTS: ASCORBIC ACID 40 mg/1 1; NIACIN 3 mg/1 1; IRON 125 mg/1 1
INACTIVE INGREDIENTS: CALCIUM ASCORBATE; ASCORBYL PALMITATE; XYLITOL; SODIUM ASCORBATE; MAGNESIUM ASCORBATE; LYSINE ACETATE; CITRUS BIOFLAVONOIDS; POTASSIUM ASCORBATE; SODIUM PYROPHOSPHATE; .BETA.-D-RIBOFURANOSE; CYSTEINE; GLUTATHIONE; HESPERADIN; HYPROMELLOSE, UNSPECIFIED; MAGNESIUM STEARATE; TITANIUM DIOXIDE; FD&C RED NO. 40; FD&C BLUE NO. 1

INTEGRA™

STATEMENT OF IDENTITY

Supplement Facts
Serving Size: 1 Capsule
Amount Per Serving |  | %DV* | % Daily Value for Pregnant or Lactating women
Vitamin C (from ProAscorb C**) | 40 mg | 44% | 33%
Vitamin B3 (from ProAscorb C**) | 3 mg | 19% | 17%
Iron; (62.5mg from Ferrous Fumarate; 62.5mg from Polysaccharide Iron Complex) | 125 mg | 694% | 463%
** ProAscorb C is a proprietary blend of; Calcium Ascorbate, Ascorbic Acid, Ascorbyl Palmitate, Niacinamide; Ascorbate, Xylitol, Sodium Ascorbate, Magnesium Ascorbate, Lysine Acetate,; Citrus Bioflavonoids, Potassium Ascorbate, Sodium Pyrophosphate,; D-Ribofuranose, L-Cysteine, Glutathione and Hesperidin | 75 mg | † | †
* Percent Daily Value based on 2000 calorie intake of adults and children 12 years and older. † Daily Value not established

Other Ingredients: Hypromellose, Magnesium Stearate, Titanium Dioxide, FD & C Red#40, FD & C Blue#1.

INDICATIONS: IntegraTM is indicated for the treatment of iron deficiency anemia, which may occur due to an increased need for iron, a deficient intake of iron, or an excessive loss of iron.

WARNINGS

WARNING: Accidental overdose of iron-containing products is a leading cause of fatal poisoning in children under 6. Keep this product out of reach of children. In case of accidental overdose, call a doctor or poison control center immediately.

HOW SUPPLIED: IntegraTM are swedish orange Vcaps® capsules printed in yellow with “Integra” on the cap and “US” logo on the body. Packed in child resistant caps and light resistant bottles of 90 capsules (52747-0710-60) and 30 capsules (52747-0710-30). The listed product numbers are not National Drug Codes. Instead, US Pharmaceutical Corporation has assigned these product codes formatted according to standard industry practice to meet the formatting requirements of pharmacy and healthcare insurance computer systems.

You should contact your healthcare provider for medical advice about adverse events. To report a serious adverse event, contact US Pharmaceutical Corporation, P.O.Box 360465,Decatur,GA 30036.

DOSAGE AND ADMINISTRATION: Adults (persons over 12 years of age), one (1) capsule daily, between meals, or as prescribed by a physician. Do not exceed recommended dosage.

SAFE HANDLING WARNING

Store at room temperature 15° to 30°C (59° to 86°F) and dry place.

Vcaps® and the Vcaps® Logo are trademarks used under license. Patent Numbers: USA: 5,626,883; Mexico MX/a/2008/004461; Singapore: 200802623-9 and other countries.

Rev.03/2022

HEALTH CLAIM

IRON / VITAMIN SUPPLEMENT CAPSULES